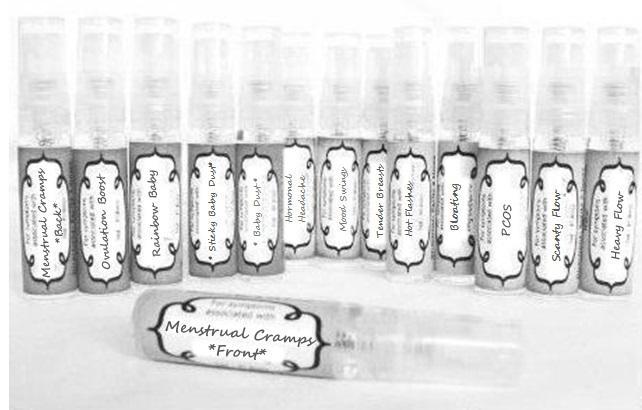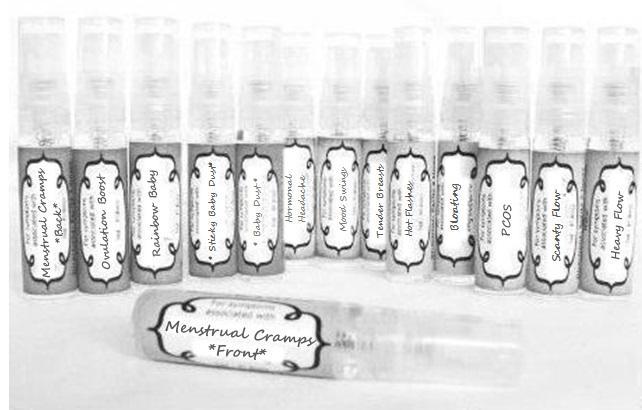 DRUG LABEL: Menstrual Cramps Front
NDC: 59667-0061 | Form: SPRAY
Manufacturer: Home Sweet Homeopathics
Category: homeopathic | Type: HUMAN OTC DRUG LABEL
Date: 20130802

ACTIVE INGREDIENTS: AMMONIUM CHLORIDE 30 [hp_C]/30 [hp_C]; ATROPA BELLADONNA 30 [hp_C]/30 [hp_C]; SELENICEREUS GRANDIFLORUS STEM 30 [hp_C]/30 [hp_C]; DIEFFENBACHIA SEGUINE 30 [hp_C]/30 [hp_C]; TRIBASIC CALCIUM PHOSPHATE 30 [hp_C]/30 [hp_C]; CAULOPHYLLUM THALICTROIDES ROOT 30 [hp_C]/30 [hp_C]; MATRICARIA RECUTITA 30 [hp_C]/30 [hp_C]; ANAMIRTA COCCULUS SEED 30 [hp_C]/30 [hp_C]; CONIUM MACULATUM FLOWERING TOP 30 [hp_C]/30 [hp_C]; GELSEMIUM SEMPERVIRENS ROOT 30 [hp_C]/30 [hp_C]; STRYCHNOS IGNATII SEED 30 [hp_C]/30 [hp_C]; STRYCHNOS NUX-VOMICA SEED 30 [hp_C]/30 [hp_C]; MAGNESIUM CHLORIDE 30 [hp_C]/30 [hp_C]; PLATINUM 30 [hp_C]/30 [hp_C]; LYCOSA TARANTULA 30 [hp_C]/30 [hp_C]; SEPIA OFFICINALIS JUICE 30 [hp_C]/30 [hp_C]; USTILAGO MAYDIS 30 [hp_C]/30 [hp_C]; VIBURNUM OPULUS BARK 30 [hp_C]/30 [hp_C]
INACTIVE INGREDIENTS: WATER; ALCOHOL

PURPOSE

For symptoms associated with

To be used according to label indications.

Directions:

Spritz 1 time under the tongue 3 x per day until improvement is seen, dose once each time symptoms return.

Keep out of reach of children.

WARNINGS

If no improvement is seen after 7 days or new symptoms develop, discontinue use.

Active ingredients:

listed for each remedy.

Inactive Ingredients:

In reverse osmosis water with less than 1% alcohol.